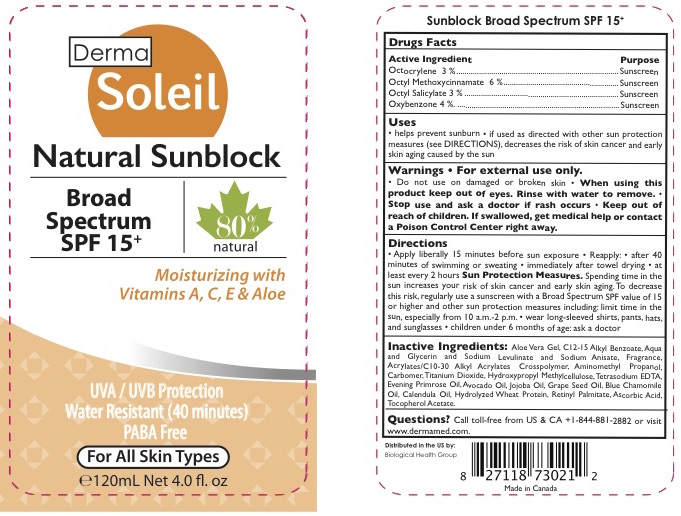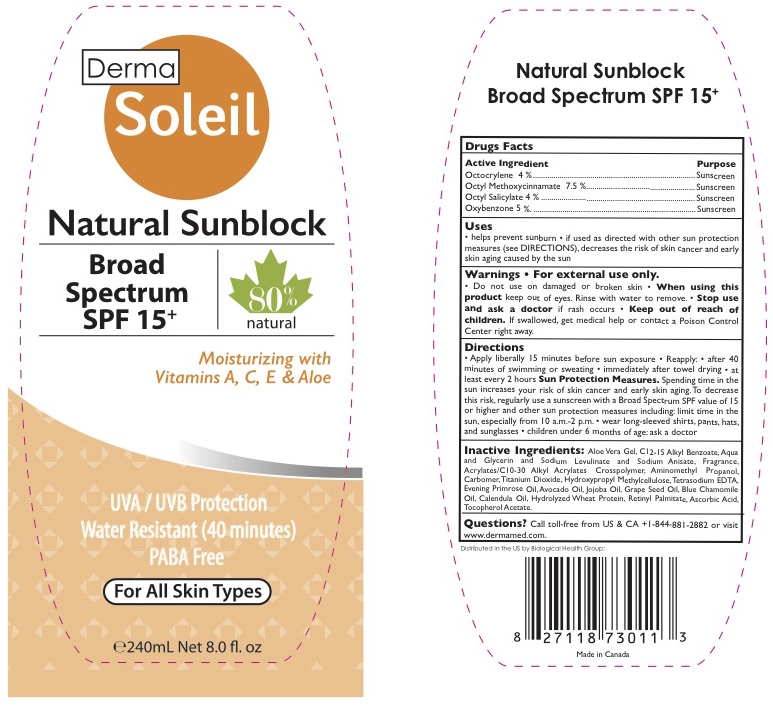 DRUG LABEL: Derma Soleil Natural Sunblock SPF 15
NDC: 69711-152 | Form: LOTION
Manufacturer: Derma Soleil
Category: otc | Type: HUMAN OTC DRUG LABEL
Date: 20170724

ACTIVE INGREDIENTS: OCTISALATE 3 g/100 mL; OXYBENZONE 4 g/100 mL; OCTINOXATE 6 g/100 mL; OCTOCRYLENE 3 g/100 mL
INACTIVE INGREDIENTS: GLYCERIN; EDETATE SODIUM; EVENING PRIMROSE OIL; JOJOBA OIL; GRAPE SEED OIL; CHAMOMILE FLOWER OIL; .ALPHA.-TOCOPHEROL ACETATE; GLYCERYL CAPRYLATE; CARBOMER COPOLYMER TYPE A (ALLYL PENTAERYTHRITOL CROSSLINKED); AVOCADO OIL; ALKYL (C12-15) BENZOATE; WATER; SODIUM LEVULINATE; SODIUM ANISATE; CARBOMER INTERPOLYMER TYPE A (55000 CPS); AMINOMETHYLPROPANOL; CARBOXYPOLYMETHYLENE; TITANIUM DIOXIDE; HYPROMELLOSES; CALENDULA OFFICINALIS FLOWER; HYDROLYZED WHEAT PROTEIN (ENZYMATIC, 3000 MW); VITAMIN A PALMITATE; ASCORBIC ACID; ALOE VERA LEAF

Derma Soleil Natural Sunblock SPF 15

Drug Facts

Active Ingredients

- Octocrylene 3%
- Octyl Methoxycinnamate 6%,
- Octyl Salicylate 3%,
- Oxybenzone 4%

Purpose

Sunscreen

Uses

- Helps prevent sunburn
- If used as directed with other sun protection measures (see Directions), decreases the risk of skin cancer and early skin aging caused by the sun.

Warnings

For external use only.

Do not use on damaged or broken skin. Stop use and ask a doctor if rash occurs.

When using this product keep out of eyes. Rinse with water to remove.

Keep out of reach of children. If swallowed, get medical help or contact a poison control center right away.

Directions

• Apply liberally 15 minutes before sun exposure • Reapply: • after 40 minutes of swimming or sweating • immediately after towel drying • at least every 2 hours
Sun Protection Measures. Spending time in the sun increases your risk of skin cancer and early skin aging.To decrease this risk, regularly use a sunscreen with a Broad Spectrum SPF value of 15 or higher and other sun protection measures including: limit time in the sun, especially from 10 a.m.-2 p.m. • wear long-sleeved shirts, pants, hats, and sunglasses • children under 6 months of age: ask a doctor

Ingredients

Aloe Vera Gel, C12-15 Alkyl Benzoate, Aqua and Glycerin and Sodium Levulinate and Sodium Anisate, Fragrance, Acrylates/C10-30 Alkyl Acrylates Crosspolymer, Aminomethyl Propanol, Carbomer, Titanium Dioxide, Hydroxypropyl Methylcellulose, Tetrasodium EDTA, Evening Primrose Oil, Avocado Oil, Jojoba Oil, Grape Seed Oil, Blue Chamomile Oil, Calendula Oil, Hydrolyzed Wheat Protein, Retinyl Palmitate, Ascorbic Acid, Tocopherol Acetate.

PRINCIPAL DISPLAY PANEL - 120 ml Tube

Derma Soleil Health

Natural Sunblock SPF 15
80% Natural

Moisturizing with Vitamins A, C, E & Aloe

UVA+UVB Protection
Water Resistant (40 minutes)
PABA Free

For All Skin Types

Broad Spectrum
SPF 15+

Net 4 fl. Oz (120 ml)

PRINCIPAL DISPLAY PANEL - 240 ml Tube

Derma Soleil Health

Natural Sunblock SPF 15
80% Natural

Moisturizing with Vitamins A, C, E & Aloe

UVA+UVB Protection
Water Resistant (40 minutes)
PABA Free

For All Skin Types

Broad Spectrum
SPF 15+

Net 8 fl. Oz (240 ml)